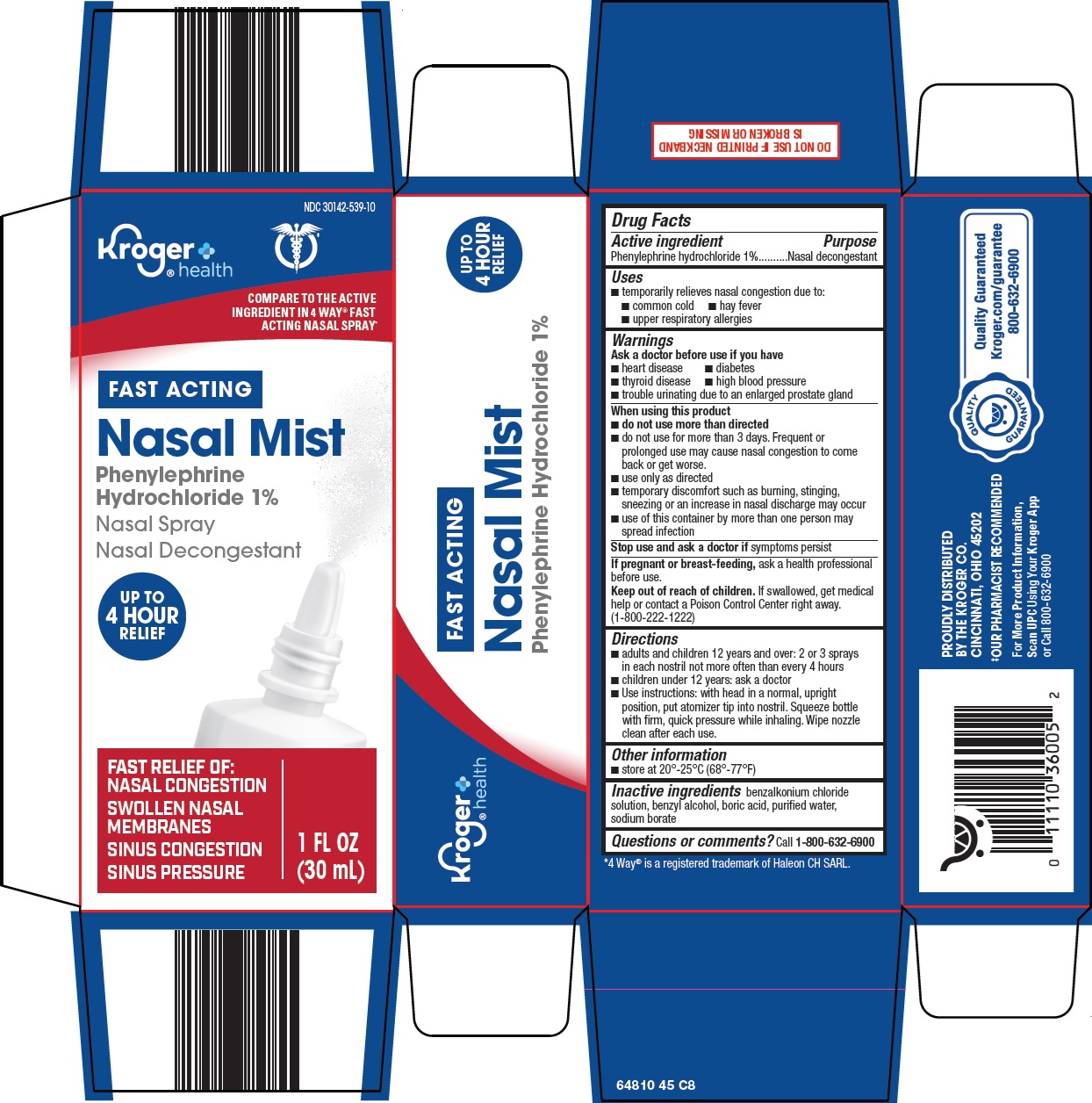 DRUG LABEL: nasal
NDC: 30142-539 | Form: SPRAY
Manufacturer: Kroger Company
Category: otc | Type: HUMAN OTC DRUG LABEL
Date: 20260212

ACTIVE INGREDIENTS: PHENYLEPHRINE HYDROCHLORIDE 1 g/100 mL
INACTIVE INGREDIENTS: BENZALKONIUM CHLORIDE; BENZYL ALCOHOL; BORIC ACID; SODIUM BORATE; WATER

Kroger Co. Nasal Mist Drug Facts

Active ingredient

Phenylephrine hydrochloride 1%

Purpose

Nasal decongestant

Uses

- temporarily relieves nasal congestion due to:
- common cold
- hay fever
- upper respiratory allergies

Warnings

Ask a doctor before use if you have

- heart disease
- diabetes
- thyroid disease
- high blood pressure
- trouble urinating due to an enlarged prostate gland

When using this product

- do not use more than directed
- do not use for more than 3 days. Frequent or prolonged use may cause nasal congestion to come back or get worse.
- use only as directed
- temporary discomfort such as burning, stinging, sneezing or an increase in nasal discharge may occur
- use of this container by more than one person may spread infection

Stop use and ask a doctor if

symptoms persist

If pregnant or breast-feeding,

ask a health professional before use.

Keep out of reach of children.

If swallowed, get medical help or contact a Poison Control Center right away. (1-800-222-1222)

Directions

- adults and children 12 years and over: 2 or 3 sprays in each nostril not more often than every 4 hours
- children under 12 years: ask a doctor
- Use instructions: with head in a normal, upright position, put atomizer tip into nostril. Squeeze bottle with firm, quick pressure while inhaling. Wipe nozzle clean after each use.

Other information

- store at 20°-25°C (68°-77°F)

Inactive ingredients

benzalkonium chloride solution, benzyl alcohol, boric acid, purified water, sodium borate

Questions or comments?

Call 1-800-632-6900

Principal Display Panel

Kroger® health

COMPARE TO THE ACTIVE INGREDIENT IN 4 WAY® FAST ACTING NASAL SPRAY

FAST ACTING

Nasal Mist

Phenylephrine Hydrochloride 1%

Nasal Spray

Nasal Decongestant

UO TO 4 HOUR RELIEF

FAST RELIEF OF:

NASAL CONGESTION

SWOLLEN NASAL MEMBRANES

SINUS CONGESTION

SINUS PRESSURE

1 FL OZ (30 mL)